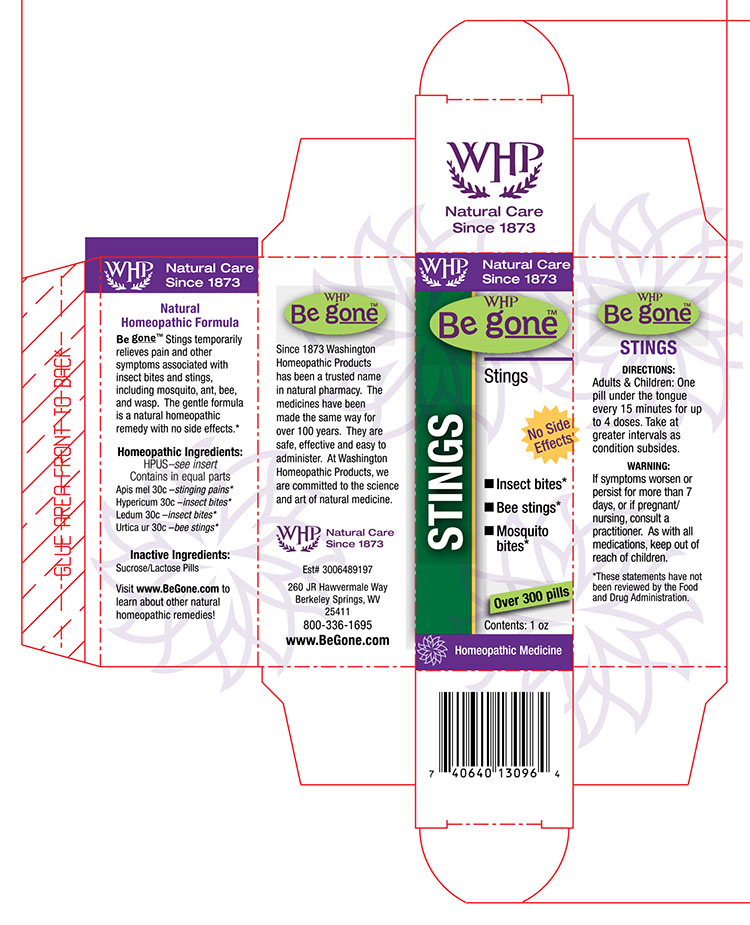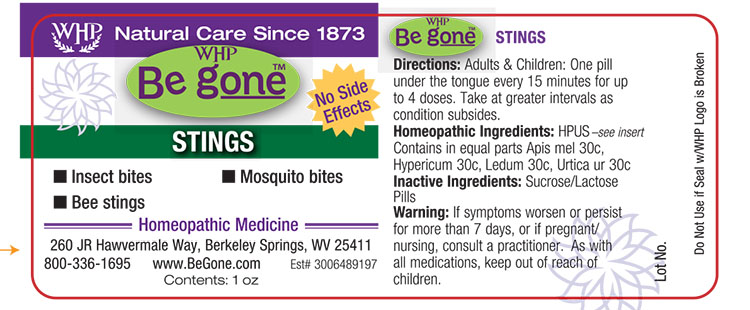 DRUG LABEL: WHP Be gone Stings
NDC: 68428-998 | Form: PELLET
Manufacturer: Washington Homeopathic Products
Category: homeopathic | Type: HUMAN OTC DRUG LABEL
Date: 20160513

ACTIVE INGREDIENTS: APIS MELLIFERA 6 [hp_C]/1 1; HYPERICUM PERFORATUM 6 [hp_C]/1 1; RHODODENDRON TOMENTOSUM LEAFY TWIG 6 [hp_C]/1 1; URTICA URENS 6 [hp_C]/1 1
INACTIVE INGREDIENTS: SUCROSE; LACTOSE

DRUG FACTS

ACTIVE INGREDIENTS

APIS MEL

HYPERICUM

LEDUM

URTICA UR

USES

Temporarily relieves pain and other symptoms associated with insect bites and stings, including mosquito, ant, bee, and wasp.

KEEP OUT OF REACH OF CHILDREN

As wtih all medications, keep out of reach of children.

INDICATIONS

Apis mel 30c –stinging pains*

Hypericum 30c –insect bites*

Ledum 30c –insect bites*

Urtica ur 30c –bee stings*

■ Insect bites ■ Bee stings ■ Mosquito bites

*These statements have not been reviewed by the Food and Drug Administration.

STOP USE AND ASK DOCTOR

If symptoms persist or recur, discontinue use. If pregnant or nursing a baby, consult a licensed practitioner before using this product.

DIRECTIONS

Adults: 2 pills every 3 hours for 2 days. Then 2 pills morning and night for 2 weeks.

Children: 1 pill. Repeat as necessary.

INACTIVE INGREDIENTS

Sucrose/Lactose Pills